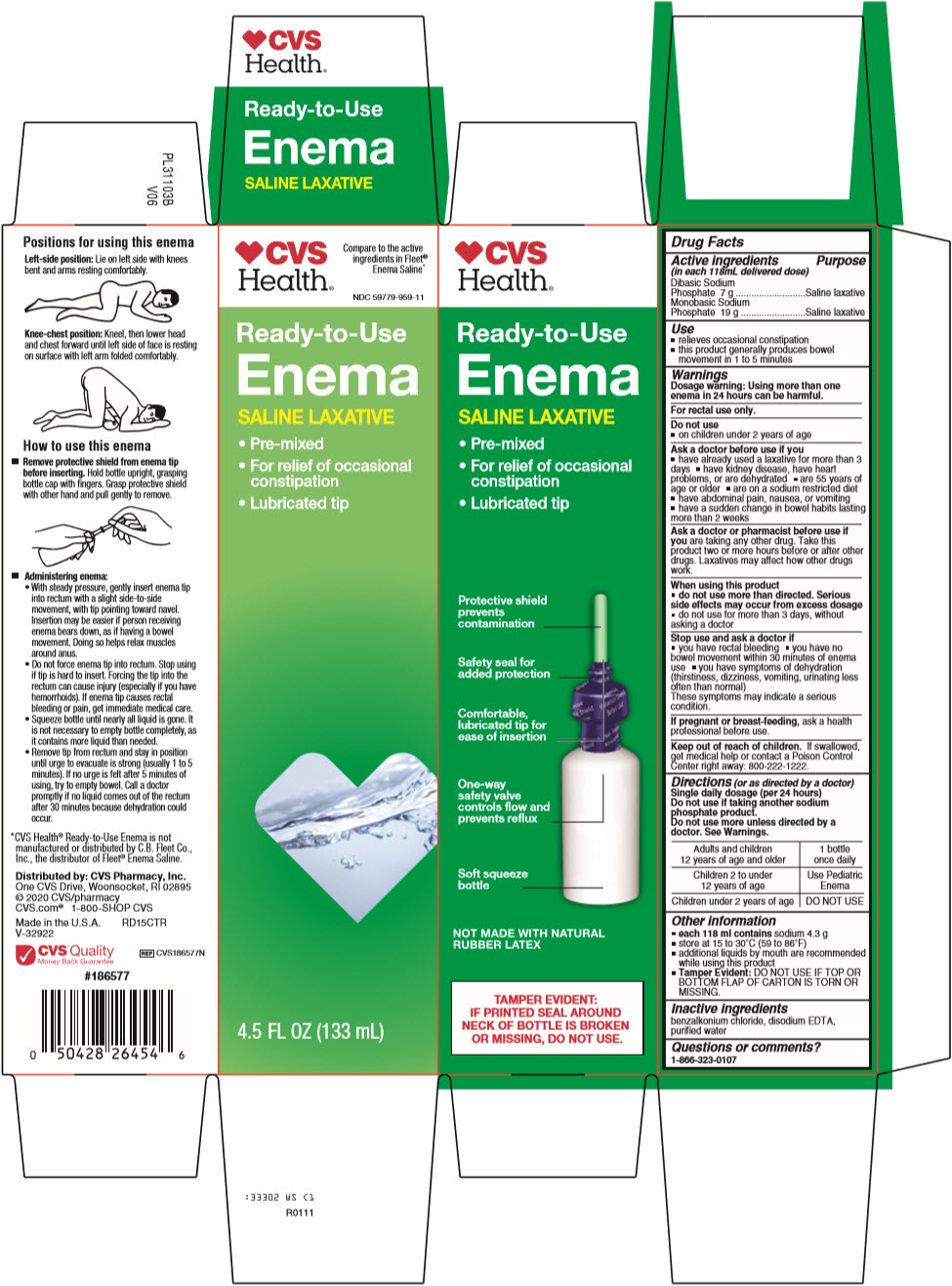 DRUG LABEL: CVS Pharmacy
NDC: 59779-959 | Form: ENEMA
Manufacturer: CVS Pharmacy
Category: otc | Type: HUMAN OTC DRUG LABEL
Date: 20260217

ACTIVE INGREDIENTS: SODIUM PHOSPHATE, DIBASIC, UNSPECIFIED FORM 7 g/118 mL; SODIUM PHOSPHATE, MONOBASIC, UNSPECIFIED FORM 19 g/118 mL
INACTIVE INGREDIENTS: BENZALKONIUM CHLORIDE; EDETATE DISODIUM; WATER

Ready-to-Use Enema SALINE LAXATIVE

Drug Facts

ACTIVE INGREDIENT

Active ingredients (in each 118mL delivered dose) | Purpose
Dibasic Sodium Phosphate 7 g | Saline laxative
Monobasic Sodium Phosphate 19 g | Saline laxative

Use

- relieves occasional constipation
- this product generally produces bowel movement in 1 to 5 minutes

Warnings

For rectal use only.

Dosage warning

Using more than one enema in 24 hours can be harmful.

Do not use

- on children under 2 years of age

Ask a doctor before use if you

- have already used a laxative for more than 3 days
- have kidney disease, have heart problems, or are dehydrated
- are 55 years of age or older
- have abdominal pain, nausea, or vomiting
- have a sudden change in bowel habits lasting more than 2 weeks

Ask a doctor or pharmacist before use if you are taking any other drug. Take this product two or more hours before or after other drugs. Laxatives may affect how other drugs work.

When using this product

- do not use more than directed. Serious side effects may occur from excess dosage
- do not use for more than 3 days, without asking a doctor

Stop use and ask a doctor if

- you have rectal bleeding
- you have no bowel movement within 30 minutes of enema use
- you have symptoms of dehydration (thirstiness, dizziness, vomiting, urinating less often than normal)

These symptoms may indicate a serious condition.

PREGNANCY OR BREAST FEEDING

If pregnant or breast-feeding, ask a health professional before use.

Keep out of reach of children. If swallowed, get medical help or contact a Poison Control Center right away: 800-222-1222.

Directions (or as directed by a doctor)

Single daily dosage (per 24 hours)

Do not use if taking another sodium phosphate product.

Do not use more unless directed by a doctor. See Warnings.

Adults and children 12 years of age and older | 1 bottle once daily
Children 2 to under 12 years of age | Use Pediatric Enema
Children under 2 years of age | DO NOT USE

Other information

- each 118 ml contains 4.3 g sodium
- store at 15 to 30°C (59 to 86°F)
- additional liquids by mouth are recommended while using this product
- Tamper Evident: DO NOT USE IF TOP OR BOTTOM FLAP OF CARTON IS TORN OR MISSING.

Inactive ingredients

benzalkonium chloride, disodium EDTA, purified water

Questions or comments?

1-866-323-0107

Distributed by: CVS Pharmacy, Inc.
One CVS Drive, Woonsocket, RI 02895

PRINCIPAL DISPLAY PANEL - 133 mL Bottle Carton

CVS
Health®

Compare to the active
ingredients in Fleet®
Enema Saline*

NDC 59779-959-11

Ready-to-Use

Enema

SALINE LAXATIVE

- Pre-mixed
- For relief of occasional
  constipation
- Lubricated tip

4.5 FL OZ (133 mL)